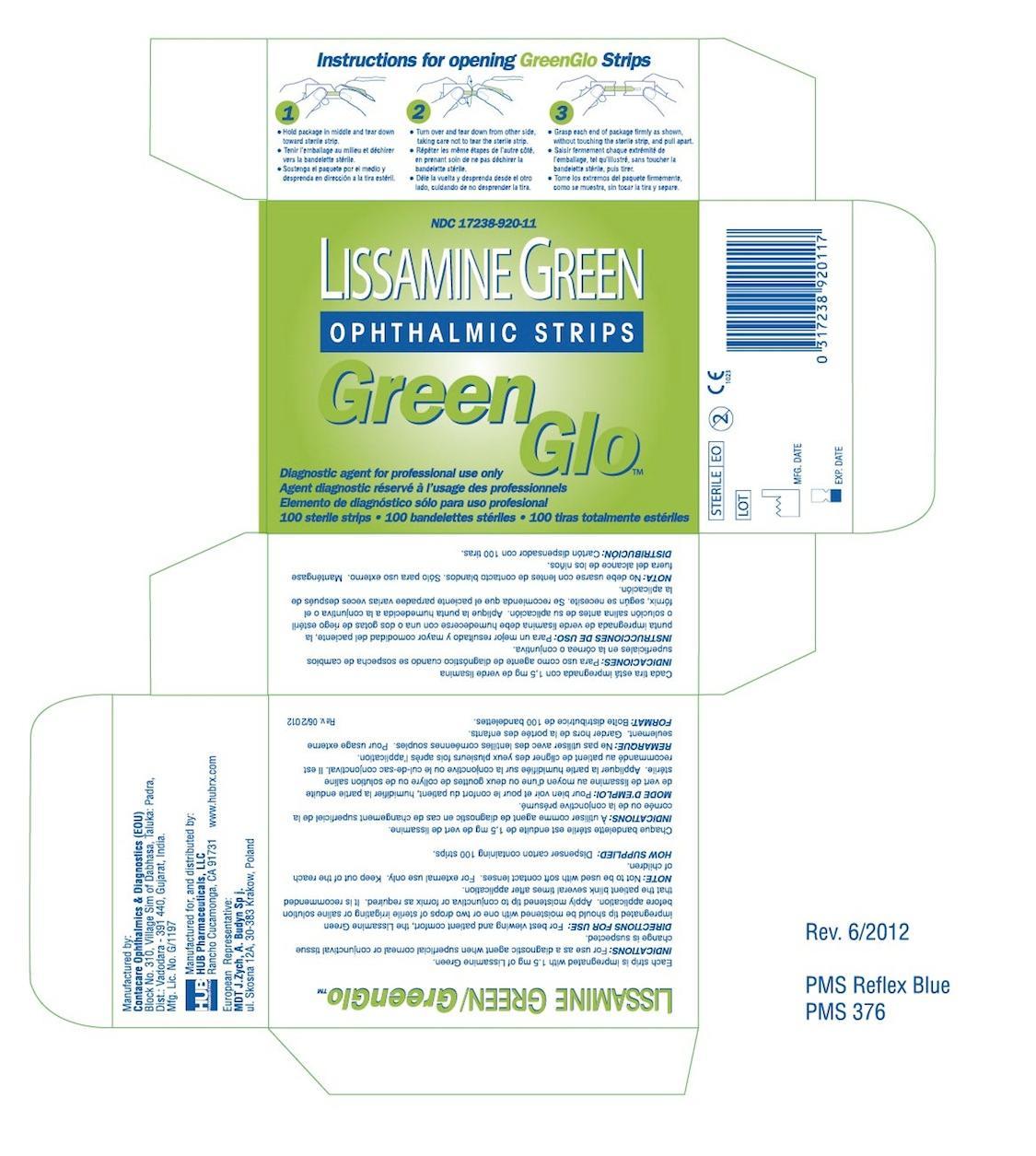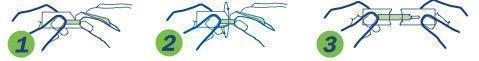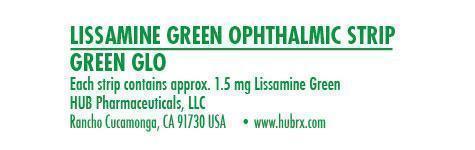 DRUG LABEL: GreenGlo
NDC: 17238-920 | Form: STRIP
Manufacturer: HUB Pharmaceuticals, Inc.
Category: prescription | Type: HUMAN PRESCRIPTION DRUG LABEL
Date: 20240101

ACTIVE INGREDIENTS: LIGHT GREEN SF YELLOWISH 1.5 mg/1.5 mg

Green Glo (Lissamine Green)

Product Facts

Each sterile strip is impregnated with 1.5 mg. of Lissamine Green

INDICATIONS:

For use as a diagnostic agent when superficial corneal or conjunctival tissue change is suspected.

DIRECTIONS FOR USE:

For best viewing and patient comfort, the Lissamine Green impregnated tip should be moistened with one or two drops of sterile irrigating or saline solution before application. Apply moistened tip to conjunctiva or fornix as required. It is recommended that the patient blink several times after application.

1. Hold package in middle and tear down toward sterile strip

2. Turn over and tear down from other side, taking care not to tear the sterile strip.

3. Grasp each end of package firmly as shown, without touching the sterile strip, and pull apart.

NOTE:

Not to be used with soft contact lenses. For external use only. Keep out of the reach of childred.

HOW SUPPLIED:

Dispenser carton containing 100 strips.

Manufactured by:

Contacare Ophthalmics & Diagnositics (EOU)

Block No. 310, Village Sim of Dabhasa, Taluka: Padra,

Dist.: Vadodara - 391 440, Gujarat, India.

Mfg. Lic. No. G/1197

Manufactured for, and distributed by:

HUB Pharmaceuticals, LLC

Rancho Cucamonga, CA 91730

www.hubrx.com

European Representative:

MDT J.Zych, A. Budyn Sp j.

ul. Skosna 12A, 30-383 Krakow, Poland

Representative Packaging:

17238-920-99: GreenGlo individual Strip (above)

17238-920-11: Dispenser Carton containing 100 strips (above)